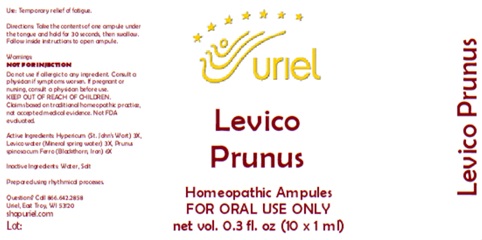 DRUG LABEL: Levico Prunus
NDC: 48951-6026 | Form: LIQUID
Manufacturer: Uriel Pharmacy Inc.
Category: homeopathic | Type: HUMAN OTC DRUG LABEL
Date: 20260227

ACTIVE INGREDIENTS: ST. JOHN'S WORT 3 [hp_X]/1 mL; FERROUS ARSENATE 3 [hp_X]/1 mL; FERRIC OXIDE RED 6 [hp_X]/1 mL; PRUNUS SPINOSA FLOWER BUD 6 [hp_X]/1 mL
INACTIVE INGREDIENTS: WATER; SODIUM CHLORIDE

Levico Prunus

PURPOSE

Use: Temporary relief of fatigue.

INDICATIONS AND USAGE

FOR ORAL USE ONLY

DOSAGE AND ADMINISTRATION

Directions: Take the contents of one ampule under the tongue and hold for 30 seconds, then swallow. Follow inside instructions to open ampule.

Warnings:
NOT FOR INJECTION
Do not use if allergic to any ingredient. Consult a physician if symptoms worsen. If pregnant or nursing, consult a physician before use.
Claims based on traditional homeopathic practice, not accepted medical evidence. Not FDA evaluated.

KEEP OUT OF REACH OF CHILDREN.

ACTIVE INGREDIENT

Active Ingredients: Hypericum (St. John’s Wort) 3X, Levico water (Mineral spring water) 3X, Prunus spinosa cum Ferro (Blackthorn, Iron) 6X

Inactive Ingredients: Water, Salt

"prepared using rhythmical processes"

QUESTIONS

Questions? Call 866.642.2858 Uriel, East Troy, WI 53120 shopuriel.com Lot: